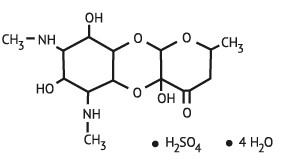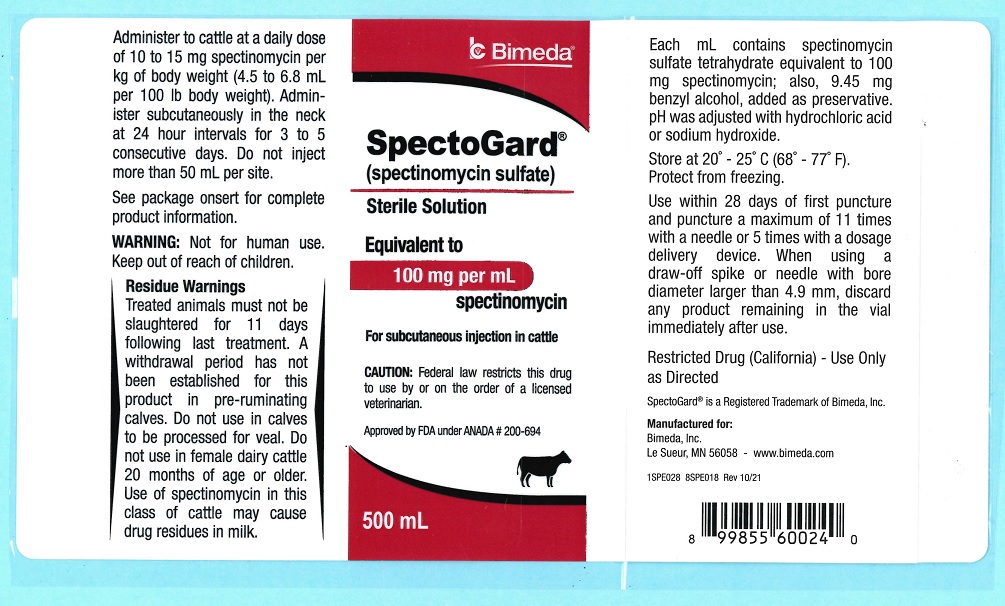 DRUG LABEL: SpectoGard
NDC: 61133-4014 | Form: INJECTION, SOLUTION
Manufacturer: Bimeda, Inc.
Category: animal | Type: PRESCRIPTION ANIMAL DRUG LABEL
Date: 20241211

ACTIVE INGREDIENTS: SPECTINOMYCIN SULFATE 100 mg/1 mL
INACTIVE INGREDIENTS: BENZYL ALCOHOL 9.45 mg/1 mL; HYDROCHLORIC ACID; SODIUM HYDROXIDE

SpectoGard®

(spectinomycin) sulfate

Sterile Solution

For subcutaneous injection in cattle

CAUTION: Federal law restricts this drug to use by or on the order of a licensed veterinarian.

DESCRIPTION

SpectoGard Sterile Solution contains the sulfate salt of spectinomycin, an aminocyclitol antibiotic produced by Streptomyces spectabilis.

Each mL of SpectoGard Sterile Solution contains spectinomycin sulfate tetrahydrate equivalent to 100 mg spectinomycin; and 9.45 mg benzyl alcohol, added as preservative. The pH was adjusted with hydrochloric acid or sodium hydroxide.

Figure 1. Chemical structure of spectinomycin sulfate tetrahydrate

The chemical name of spectinomycin sulfate tetrahydrate is: Decahydro-4a,7,9-trihydroxy-2-methyl-6,8-bis (methylamino)-4H-pyrano [2,3-b] [1,4] benzodioxin-4-one sulfate, tetrahydrate.

CLINICAL PHARMACOLOGY

Microbiology

Spectinomycin is bacteriostatic and exerts its antibacterial effect by binding to the 30S ribosome and inhibiting bacterial protein synthesis.

Spectinomycin has activity against a variety of gram-negative bacteria, some mycoplasma, and a limited number of gram-positive bacteria. Generally, it is not active against anaerobic bacteria.

Spectinomycin has demonstrated in vitro and in vivo activity against the three major pathogenic bacteria (Mannheimia haemolytica, Pasteurella multocida, and Histophilus somni) associated with bovine respiratory disease (pneumonia).

Spectinomycin has also demonstrated in vitro activity against Actinomyces pyogenes, Mycoplasma bovis, and Mycoplasma dispar. The clinical significance of this in vitro activity in cattle has not been demonstrated.

INDICATIONS AND USAGE

SpectoGard Sterile Solution is indicated for the treatment of bovine respiratory disease (pneumonia) associated with Mannheimia haemolytica, Pasteurella multocida, and Histophilus somni.

CONTRAINDICATIONS

AS with all drugs, the use of SpectoGard Sterile Solution is contraindicated in animals previously found to be hypersensitive to the drug.

Residue Warnings
Treated cattle must not be slaughtered for 11 days following last treatment. Dosages administered either in excess of the approved maximum dose or by unapproved routes may result in illegal residues in edible tissues.

A withdrawal period has not been established for this product in pre-ruminating calves. Do not use in calves to be processed for veal.

A milk discard period has not been established for this product in lactating dairy cattle. Do not use in female dairy cattle 20 months of age or older. Use of spectinomycin in this class of cattle may cause drug residues in milk.

Human Warnings

NOT FOR HUMAN USE. KEEP OUT OF REACH OF CHILDREN.

As with other antibiotics, allergic reactions may occur in previously sensitized individuals. Repeated or prolonged exposure may lead to sensitization. Avoid direct contact with skin, eyes, mouth, and clothing. Persons with a known hypersensitivity to spectinomycin should avoid exposure to this product.

In case of accidental eye exposure, flush with water for 15 minutes. In case of accidental skin exposure, wash with soap and water. Seek medical attention if allergic reactions occur.

The safety data sheet (SDS) contains more detailed occupational safety information. To report suspected adverse drug events, for technical assistance or to obtain a copy of the Safety Data Sheet, contact Bimeda, Inc. at 1-888-524-6332. For additional information about adverse drug experience reporting for animal drugs, contact FDA at 1-888-FDA-VETS or http://www.fda.gov/reportanimalae.

PRECAUTIONS

The safety of SpectoGard Sterile Solution has not been determined for cattle intended for breeding.

Discoloration at the injection site may persist beyond 11 days after injection. This may necessitate trimming of the injection site and surrounding tissues at slaughter.

ADVERSE REACTIONS

The use of SpectoGard (spectinomycin sulfate) Sterile Solution may result in mild swelling at the injection site.Anaphylactic reactions may occur in animals previously sensitized.

DOSAGE AND ADMINISTRATION

SpectoGard Sterile Solution is to be administered to cattle at a daily dose of 10 to 15 mg spectinomycin per kg of body weight (4.5 to 6.8 mL per 100 lb body weight). Treatment should be administered at 24-hour intervals for 3 to 5 consecutive days. Selection of dose (10 to 15 mg/kg/day) and duration of treatment (3 to 5 days) should be based on an assessment of the severity of disease, pathogen susceptibility, and clinical response. Do not inject more than 50 mL per site.

SpectoGard Sterile Solution is to be administered to cattle by subcutaneous injection in the neck.

ANIMAL SAFETY

Cattle: When spectinomycin sulfate sterile solution was administered at 10 times (150 mg/kg/day) the maximum daily recommended therapeutic dose for 5 days, treatment-related effects included increased relative kidney weights in heifers and steers, squamous and transitional epithelial cells in the urine of steers, and decreased urinary pH in steers. Urinalysis was not performed on the heifers in this study. Minimal injection site reactions were also present at 1 day and 4 days post injection.

When spectinomycin sulfate sterile solution was administered at doses of 14, 45, or 75 mg/kg/day (1X, 3X, or 5X the maximum daily recommended therapeutic dose) for 15 days, treatment-related effects included decreased urinary pH and mild swelling at injection sites. At necropsy, labeled injection sites examined at 1 day and 8 days after injection of 30 mL of spectinomycin sulfate sterile solution had dark red, tan, brown, and/or dark brown areas, often with some expansion (thickening) of the subcutis. Only mild discoloration was observed on gross examination of injection sites at 15 days after injection.

When spectinomycin sulfate sterile solution was administered subcutaneously at a dose of 15 mg/kg/day to 152 crossbred beef calves with naturally occurring BRD in clinical field trials, one calf died following the second daily injection. The cause of death following a gross necropsy was reported as an anaphylactic reaction.

STORAGE CONDITIONS

Store at 20° - 25° C (68° - 77° F). Protect from freezing. Use within 28 days of first puncture and puncture a maximum of 11 times with a needle or 5 times with a dosage delivery device. When using a draw-off spike or needle with bore diameter larger than 4.9 mm, discard any product remaining in the vial immediately after use.

HOW SUPPLIED

SpectoGard Sterile Solution is available in the following package size: 500 mL Multi-Dose vial.

Approved by FDA under ANADA # 200-694

Restricted Drug (California) – Use Only as Directed

Manufactured for:

Bimeda, Inc.

Le Sueur, MN 56058

www.bimeda.com